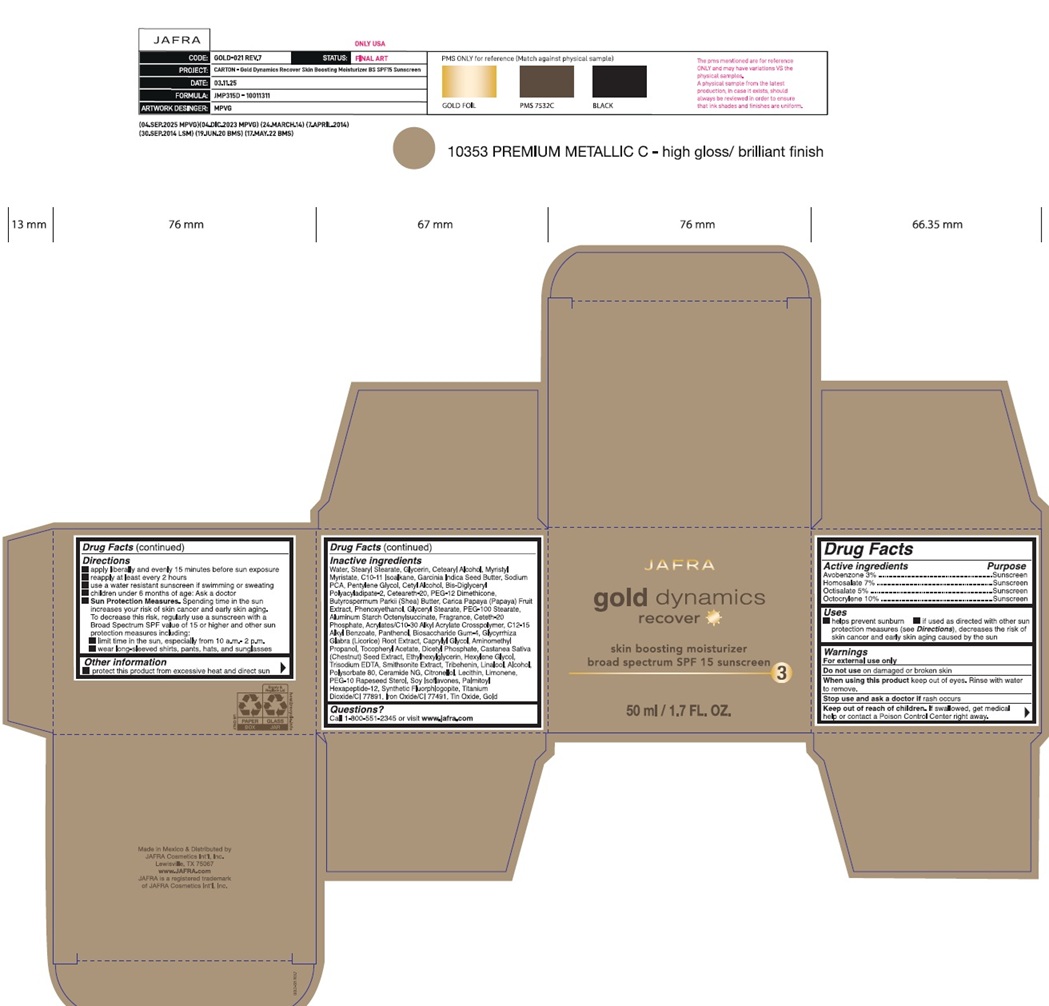 DRUG LABEL: Gold Dynamics Skin Boosting Moisturizer Broad Spectrum SPF 15 Sunscreen
NDC: 68828-643 | Form: CREAM
Manufacturer: Distribuidora Comercial Jafra, S.A. de C.V.
Category: otc | Type: HUMAN OTC DRUG LABEL
Date: 20251119

ACTIVE INGREDIENTS: AVOBENZONE 3 g/100 mL; HOMOSALATE 7 g/100 mL; OCTISALATE 5 g/100 mL; OCTOCRYLENE 10 g/100 mL
INACTIVE INGREDIENTS: WATER; STEARYL STEARATE; GLYCERIN; CETOSTEARYL ALCOHOL; MYRISTYL MYRISTATE; C10-11 ISOPARAFFIN; GARCINIA INDICA SEED BUTTER; SODIUM PYRROLIDONE CARBOXYLATE; PENTYLENE GLYCOL; CETYL ALCOHOL; BIS-DIGLYCERYL POLYACYLADIPATE-2; POLYOXYL 20 CETOSTEARYL ETHER; PEG-12 DIMETHICONE (300 CST); SHEA BUTTER; PAPAYA; PHENOXYETHANOL; GLYCERYL MONOSTEARATE; PEG-100 MONOSTEARATE; ALUMINUM STARCH OCTENYLSUCCINATE; CETETH-20 PHOSPHATE; ACRYLATES/C10-30 ALKYL ACRYLATE CROSSPOLYMER (60000 MPA.S); ALKYL (C12-15) BENZOATE; PANTHENOL; BIOSACCHARIDE GUM-4; GLYCYRRHIZA GLABRA (LICORICE) ROOT POWDER; CAPRYLYL GLYCOL; AMINOMETHYLPROPANOL; .ALPHA.-TOCOPHEROL ACETATE; DIHEXADECYL PHOSPHATE; SPANISH CHESTNUT; ETHYLHEXYLGLYCERIN; HEXYLENE GLYCOL; EDETATE TRISODIUM; TRIBEHENIN; LINALOOL, (+/-)-; ALCOHOL; POLYSORBATE 80; CERAMIDE NG; .BETA.-CITRONELLOL, (R)-; LECITHIN, SOYBEAN; LIMONENE, (+)-; PEG-10 RAPESEED STEROL; SOY ISOFLAVONES; PALMITOYL HEXAPEPTIDE-12; MAGNESIUM POTASSIUM ALUMINOSILICATE FLUORIDE; TITANIUM DIOXIDE; FERRIC OXIDE RED; STANNIC OXIDE; GOLD

Active ingredients

Avobenzone 3%
Homosalate 7%
Octisalate 5%
Octocrylene 10%

Purpose

Sunscreen

Uses

• helps prevent sunburn
• if used as directed with other sun protection measures (see Directions), decreases the risk of skin cancer and early skin aging caused by

the sun

Warnings

- For external use only
- Do not useon damaged or broken skin
- When using this productkeep out of eyes. Rinse with water to remove.
- Stop use and ask a doctor ifrash occurs
- Keep out of reach of children. If swallowed, get medical help or contact a Poison Control Center right away.

Directions

• apply liberally and evenly 15 minutes before sun exposure

• reapply at least every 2 hours

• use a water resistant sunscreen if swimming or sweating

• children under 6 months of age: Ask a doctor

- Sun Protection Measures. Spending time in the sun increases your risk of skin cancer and early skin aging. To decrease this risk, regularly use a sunscreen with a Broad Spectrum SPF value of 15 or higher and other sun protection measures including:

• limit time in the sun, especially from 10 a.m. – 2 p.m.
• wear long-sleeved shirts, pants, hats, and sunglasses

Other information

• protect this product from excessive heat and direct sun

Inactive ingredients

Water, Stearyl Stearate, Glycerin, Cetearyl Alcohol, Myristyl Myristate, C10-11 Isoalkane, Garcinia Indica Seed Butter, Sodium PCA, Pentylene Glycol, Cetyl Alcohol, Bis-Diglyceryl Polyacyladipate-2, Ceteareth-20, PEG-12 Dimethicone, Butyrospermum Parkii (Shea) Butter, Carica Papaya (Papaya) Fruit Extract, Phenoxyethanol, Glyceryl Stearate, PEG-100 Stearate, Aluminum Starch Octenylsuccinate, Fragrance, Ceteth-20
Phosphate, Acrylates/C10-30 Alkyl Acrylate Crosspolymer, C12-15 Alkyl Benzoate, Panthenol, Biosaccharide Gum-4, Glycyrrhiza Glabra (Licorice) Root Extract, Caprylyl Glycol, Aminomethyl Propanol, Tocopheryl Acetate, Dicetyl Phosphate, Castanea Sativa (Chestnut) Seed Extract, Ethylhexylglycerin, Hexylene Glycol, Trisodium EDTA, Smithsonite Extract, Tribehenin, Linalool, Alcohol, Polysorbate 80, Ceramide NG, Citronellol, Lecithin, Limonene, PEG-10 Rapeseed Sterol, Soy Isoflavones, Palmitoyl Hexapeptide-12, Synthetic Fluorphlogopite, Titanium Dioxide/CI 77891, Iron Oxide/CI 77491, Tin Oxide, Gold

Questions?

Call 1-800-551-2345 or visit www.jafra.com